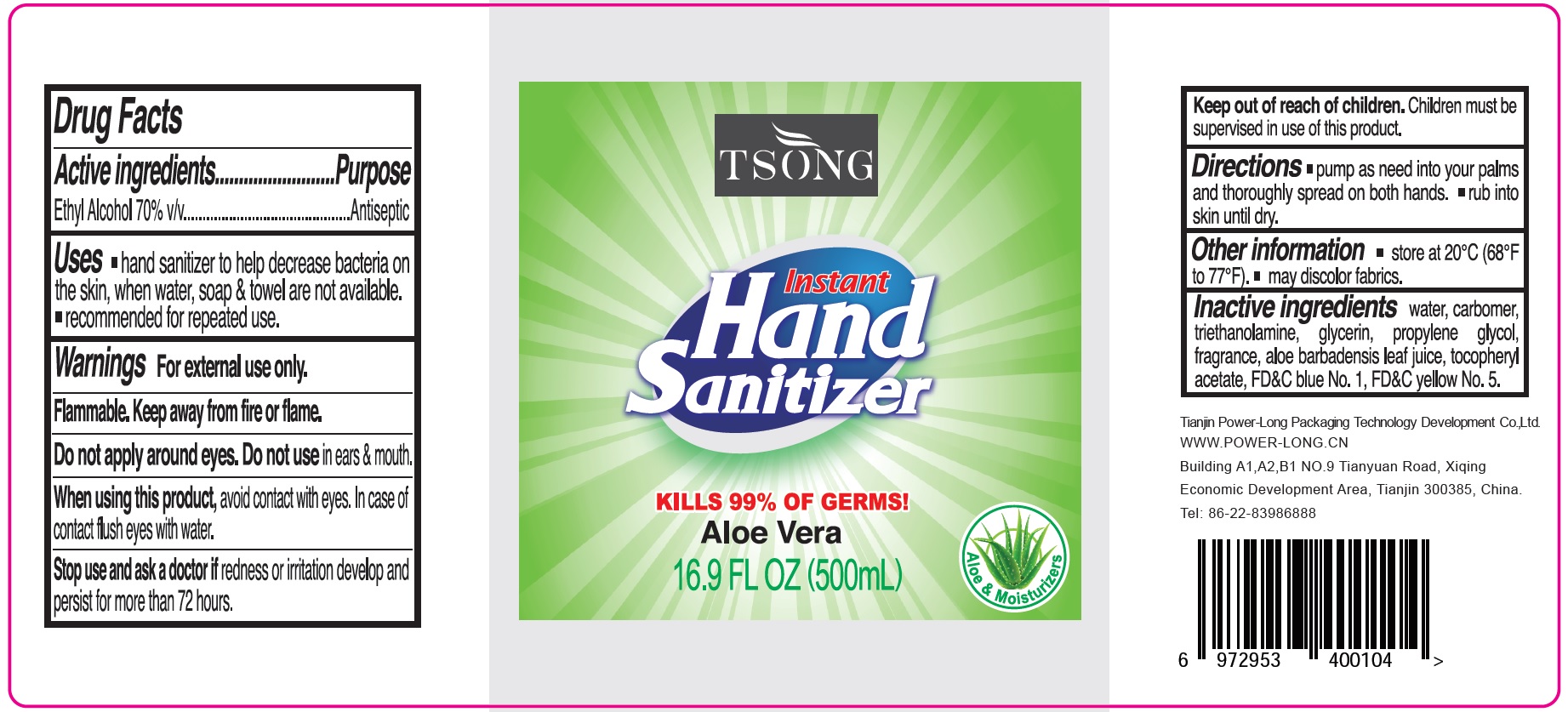 DRUG LABEL: TSONG Hand Sanitizer
NDC: 79035-002 | Form: GEL
Manufacturer: Tianjin Power-Long Packaging Technology Development Co.,Ltd.
Category: otc | Type: HUMAN OTC DRUG LABEL
Date: 20231023

ACTIVE INGREDIENTS: ALCOHOL 0.7 mL/1 mL
INACTIVE INGREDIENTS: WATER; CARBOMER HOMOPOLYMER, UNSPECIFIED TYPE; TROLAMINE; GLYCERIN; PROPYLENE GLYCOL; ALOE VERA LEAF; .ALPHA.-TOCOPHEROL ACETATE; FD&C BLUE NO. 1; FD&C YELLOW NO. 5

TSONG Hand Sanitizer

Active ingredients

Ethyl Alcohol 70% v/v

Purpose

Antiseptic

Uses

- hand sanitizer to help decrease bacteria on the skin, when water, soap & towel are not available.
- recommended for repeated use.

Warnings

For external use only.

Flammable. Keep away from fire or flame.

Do not apply around eyes.

Do not use

in ears & mouth

When using this product,

avoid contact with eyes. In case of contact, flush eyes with water.

Stop use and ask a doctor if

redness or irritation develop and persist for more than 72 hours.

Keep out of reach of children.

Children must be supervised in use of this product.

Directions

- pump as need into your palms and thoroughly spread on both hands.
- rub into skin until dry.

Other information

- store at 20°C (68°F to 77°F).
- may discolor fabrics.

Inactive ingredients

water, carbomer, triethanolamine, glycerin, propylene glycol, fragrance, alow barbadensis leaf juice, tocopheryl acetate, FD&C blue No.1, FD&C yellow No.5.